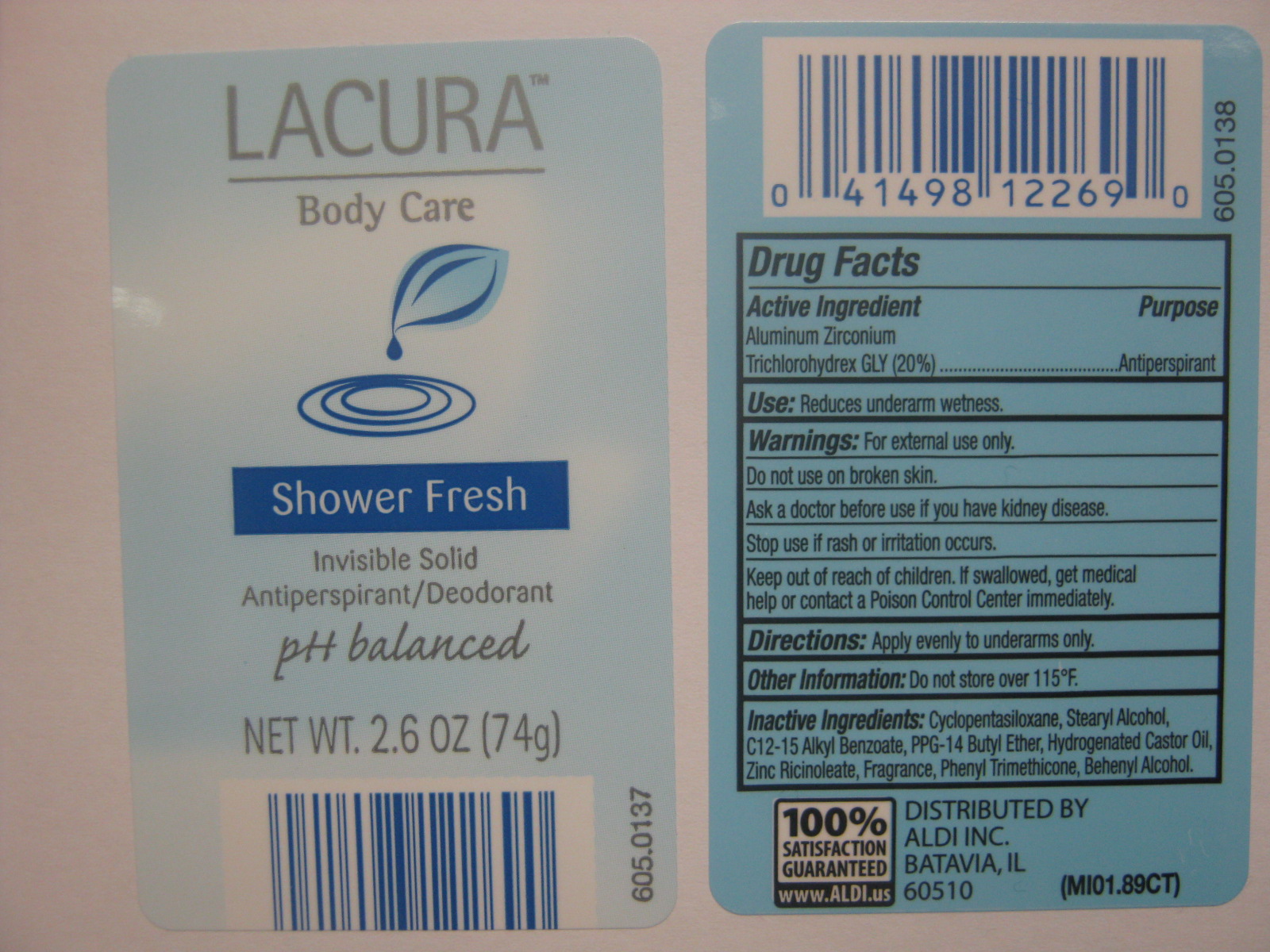 DRUG LABEL: Lacura Invisible Solid Shower Fresh
NDC: 10889-113 | Form: STICK
Manufacturer: VVF Kansas Services LLC
Category: otc | Type: HUMAN OTC DRUG LABEL
Date: 20101117

ACTIVE INGREDIENTS: ALUMINUM ZIRCONIUM TRICHLOROHYDREX GLY 250 mg/1 g
INACTIVE INGREDIENTS: Stearyl Alcohol; Hydrogenated Castor Oil; Phenyl Trimethicone; C12-15 Alkyl Benzoate; Zinc Ricinoleate; Docosanol

Lacura Invisible Solid Shower Fresh (Aluminun Zirconium Trichlorohydrex Gly)

ACTIVE INGREDIENT

Aluminum Zirconium Trichlorohydrex Gly 20%

PURPOSE

Anti-perspirant

USES

Reduces underarm wetness.

WARNINGS

For external use only.

Do not use on broken skin.

Ask a doctor before you use if you have kidney disease.

Stop use if rash or irritation occurs.

Keep out of reach of children.

If swallowed get medical help or contact a Poison Control Center immediately.

Directions

Apply evenly to underarms only.

STORAGE AND HANDLING

Do not store over 115 degrees F

Inactive Ingredients

Cyclopentasiloxane, Stearyl Alcohol, C12-15 Alkyl Benzoate, PPG-14 Butyl Ether, Hydrogenated Castor Oil, Zinc Ricinoleate, Fragrance, Phenyl Trimethicone, Behenyl alcohol.

Distributed By:

ALDI INC.
BATAVIA, IL
60510
(MI01.89CT)
100% Satisfaction Guaranteed
www.ALDI.us

KEEP OUT OF REACH OF CHILDREN

If swallowed, get medical help or contact a Poison Control Center immediately.

PACKAGE LABEL

Lacura
Body Care
Shower Fresh
Invisible Solid
Antiperspirant/Deodorant
pH balanced
NET WT. 2.6OZ (74g)